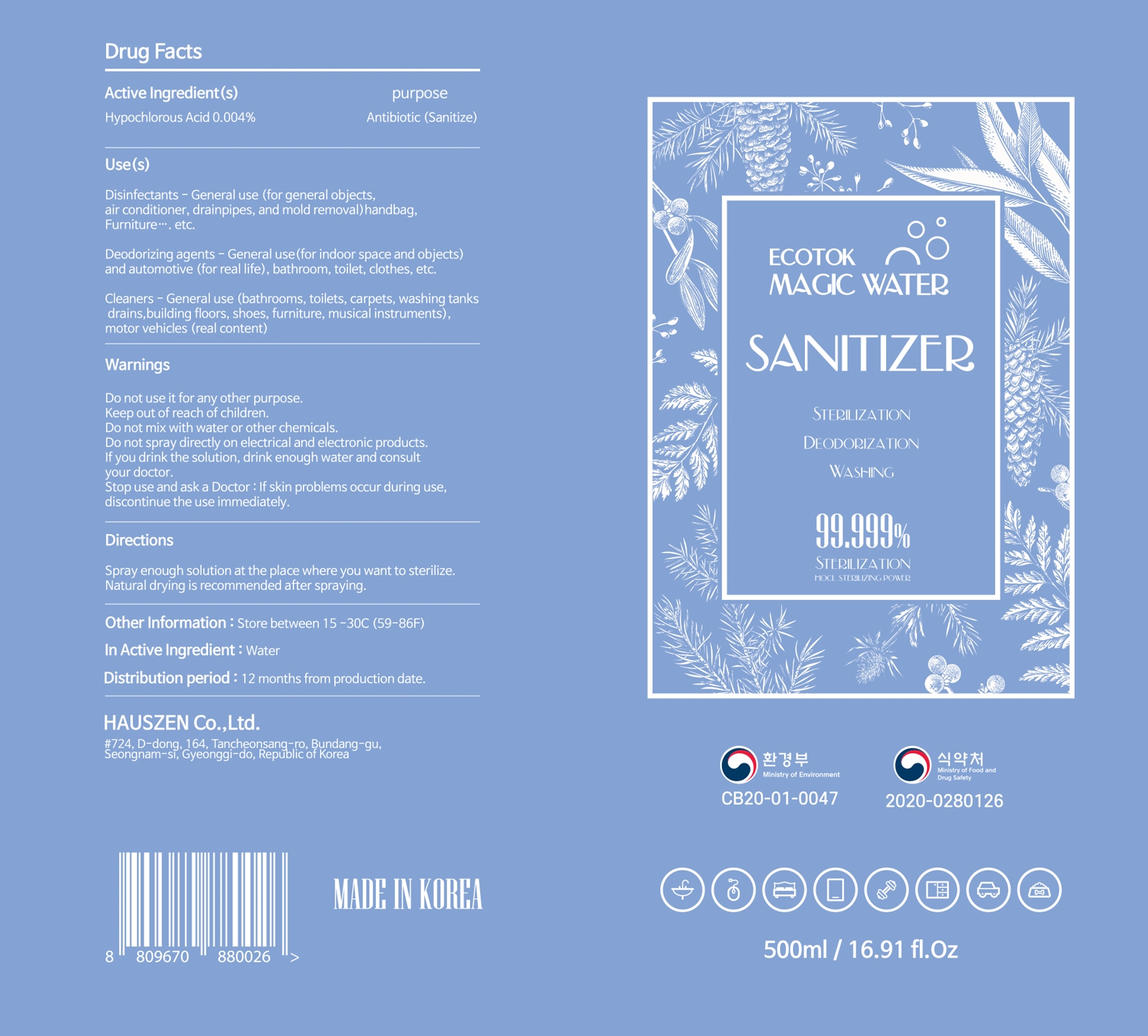 DRUG LABEL: ECOTOK MAGIC WATER
NDC: 78626-201 | Form: LIQUID
Manufacturer: HAUSZEN CO., LTD
Category: otc | Type: HUMAN OTC DRUG LABEL
Date: 20200603

ACTIVE INGREDIENTS: HYPOCHLOROUS ACID 0.004 g/100 mL
INACTIVE INGREDIENTS: WATER

ACTIVE INGREDIENT(S)

Hypochlorous Acid 0.004%

PURPOSE

Antibiotic (Sanitize)

USE(S)

Disinfectants - General use (for general objects, air conditioner, drainpipes, and mold removal) handbag, Furniture, etc.

Deodorizing agents - General use (for indoor space and objects) and automotive (for real life), bathroom, toilet, clothes, etc.

Cleaners - General use (bathrooms, toilets, carpets, washing tanks drains, building floors, shoes, furniture, musical instruments), motor vehicles (real content)

WARNINGS

Do not use it for any other purpose.

WARNINGS

Do not mix with water or other chemicals.

Do not spary directly on electrical and electronic products.

WARNINGS

Keep out of reach of children.

WARNINGS

If you drink the solution, drink enough water and consult your doctor.

Stop use and ask a Doctor: If skin problems occur during use, discontinue the use immediately.

DIRECTIONS

Spray enough solution at the place where you want to sterilize.

Natural drying is recommended after spraying.

OTHER INFORMATION

Store between 15-30C (59-86F)

INACTIVE INGREDIENT

Water